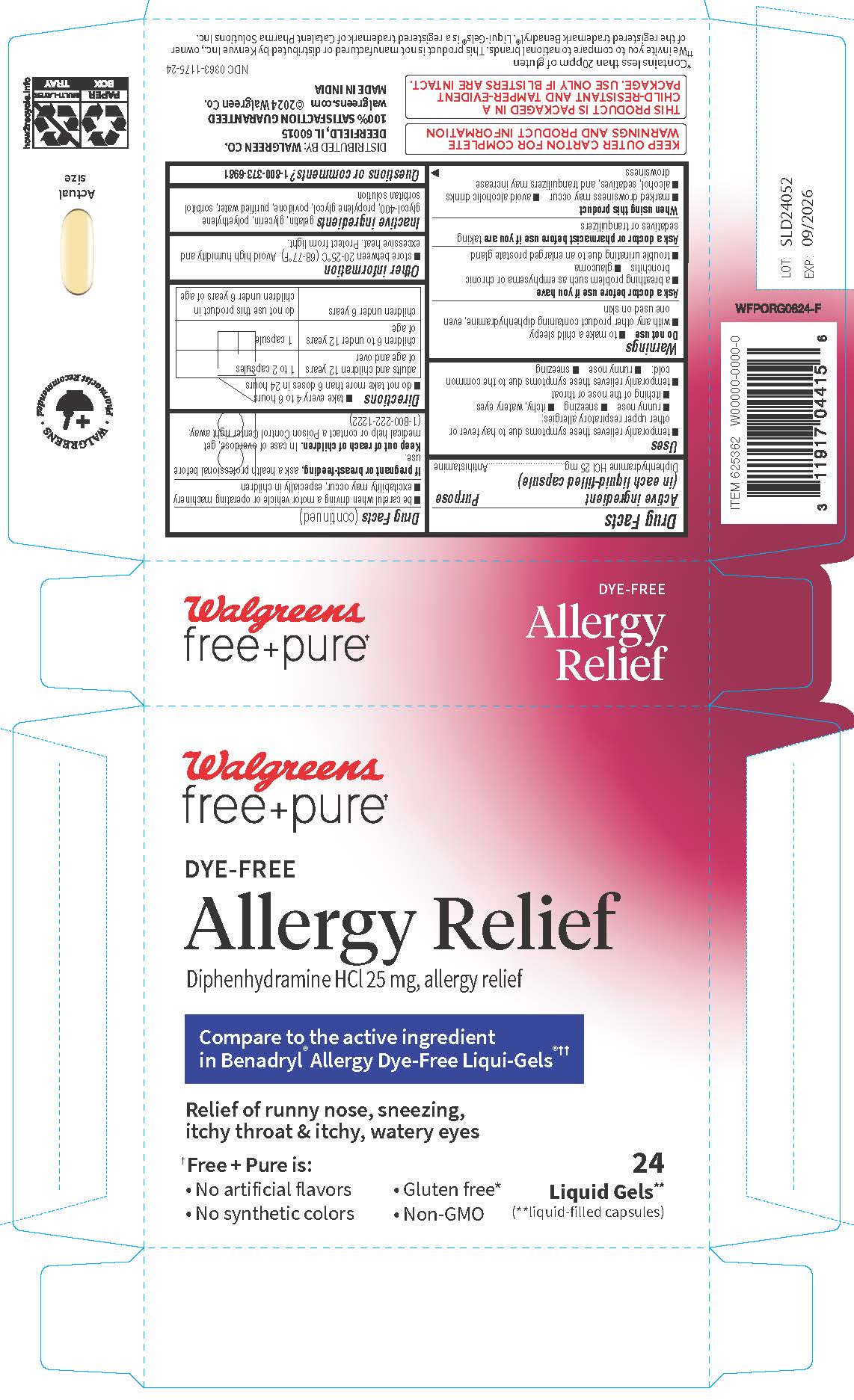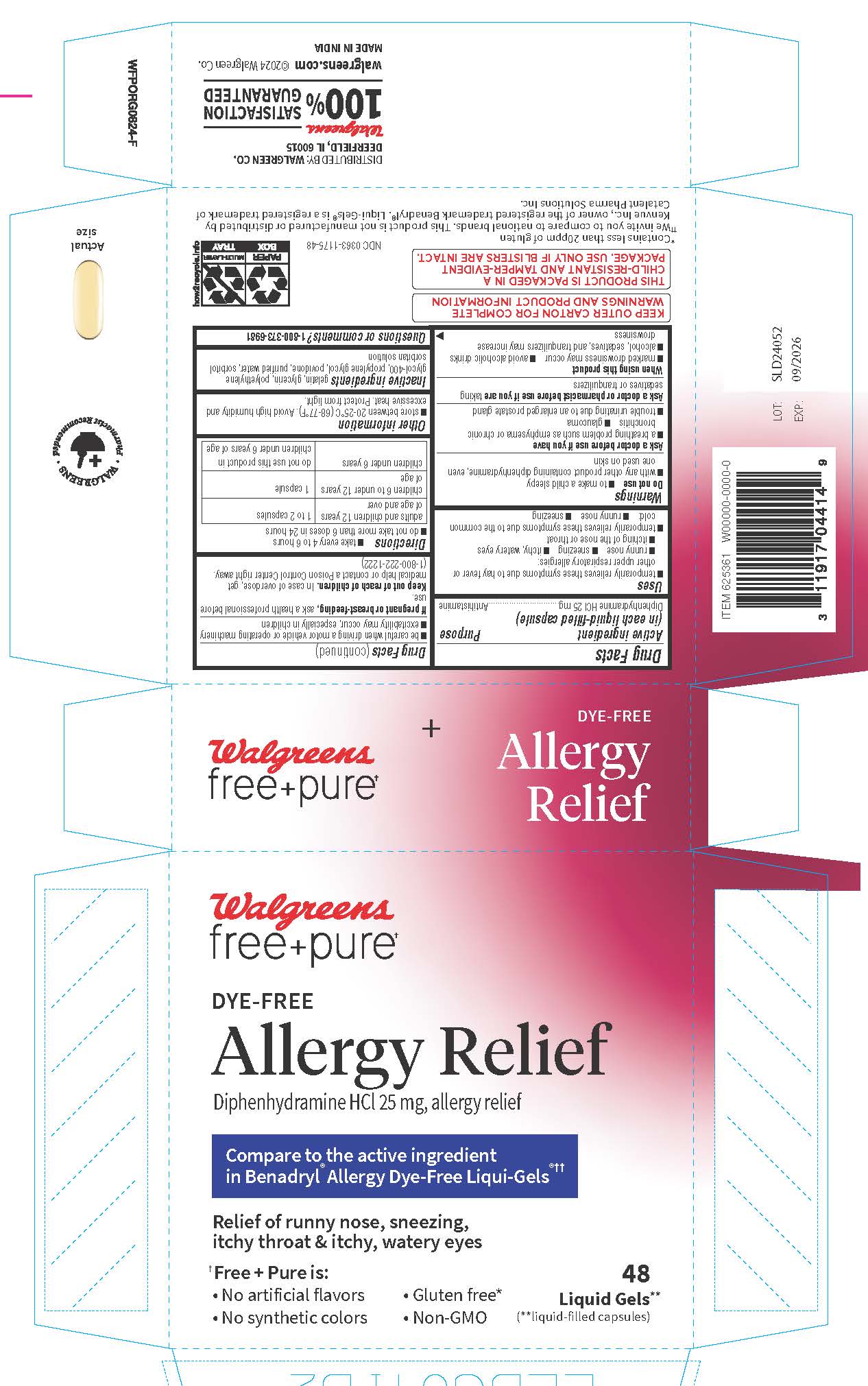 DRUG LABEL: Free and Pure Allergy Relief
NDC: 0363-1175 | Form: CAPSULE, LIQUID FILLED
Manufacturer: WALGREEN COMPANY
Category: otc | Type: HUMAN OTC DRUG LABEL
Date: 20251031

ACTIVE INGREDIENTS: DIPHENHYDRAMINE HYDROCHLORIDE 25 mg/1 1
INACTIVE INGREDIENTS: GLYCERIN; GELATIN; POLYETHYLENE GLYCOL 400; POVIDONE; WATER; SORBITOL; SORBITAN

Free and Pure Allergy Relief Dye-Free

Active ingredient (in each softgel)

Diphenhydramine HCl 25 mg

Purpose

Antihistamine

Uses

- temporarily relieves these symptoms due to hay fever or other upper respiratory allergies: sneezing, runny nose, itchy, watery eyes, itching of the nose or throat
- temporarily relieves these symptoms due to common cold: runny nose, sneezing

Warnings

Do not use

- to make a child sleepy
- with any other product containing diphenhydramine, even one used on skin

Ask a doctor before use if you have

- a breathing problem such as emphysema or chronic bronchitis
- glaucoma
- trouble urinating due to an enlarged prostate gland

Ask a doctor or pharmacist before use if you are

taking sedatives or tranquilizers.

When using this product

- marked drowsiness may occur
- avoid alcoholic drinks
- alcohol, sedatives, and tranquilizers may increase drowsiness
- be careful when driving a motor vehicle or operating machinery
- excitability may occur, especially in children

If pregnant or breast-feeding,

ask a health professional before use.

Keep out of reach of children.

In case of overdose, get medical help or contact a Poison Control Center right away. (1-800-222-1222)

Directions

- take every 4 to 6 hours
- do not take more than 6 doses in 24 hours
- adults and children 12 years of age and over - take 1 to 2 softgels
- children 6 to under 12 years of age - take 1 softgel
- children under 6 years of age - do not use

Other information

- store between 20-25ºC (68 to 77°F). Avoid high humidityandexcessive heat.
- Protect from light, heat, humidity

Inactive ingredients

gelatin, glycerin, polyethylene glycol-400, propylene glycol, povidone, purified water, sorbitol sorbitan solution

Questions or comments?

1-800-373-6981

Distributed By:
Walgreen Co.
200 Wilmot Rd., Deerfield, IL 60015

PRINCIPAL DISPLAY PANEL

Free & Pure Dye-Free
Allergy Relief

Diphenhydramine HCl 25 mg/Antihistamine
Relieves:
Sneezing
Itchy throat
Runny nose
Itchy, watery eyes